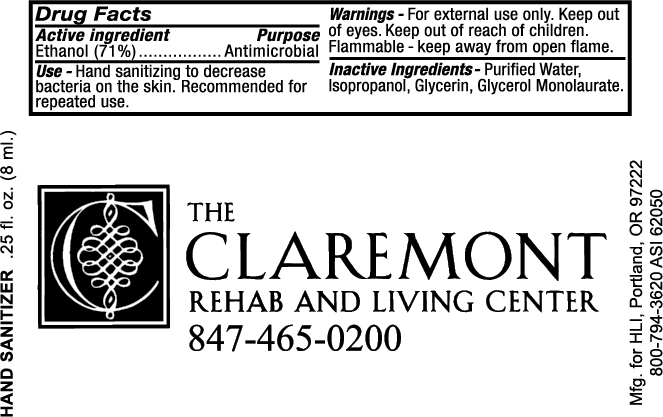 DRUG LABEL: Hand Sanitizer
								
NDC: 19392-100 | Form: LIQUID
Manufacturer: Humphreyline
Category: otc | Type: HUMAN OTC DRUG LABEL
Date: 20120621

ACTIVE INGREDIENTS: ALCOHOL 710 g/1000 mL
INACTIVE INGREDIENTS: water; isopropyl alcohol; glycerin; glyceryl laurate

Drug Facts

ACTIVE INGREDIENT

Ethanol (71%)

PURPOSE

Antimicrobial

INDICATIONS AND USAGE

Hand sanitizing to decrease bacteria on the skin. Recommended for repeated use.

WARNINGS

For external use only. Keep out of eyes. Keep out of reach of children. Flammable-keep away from open flame.

INACTIVE INGREDIENT

Purified water, isopropanol, glycerin, glycerol monolaurate

Keep out of reach of children

DOSAGE AND ADMINISTRATION

Recommended for repeated use